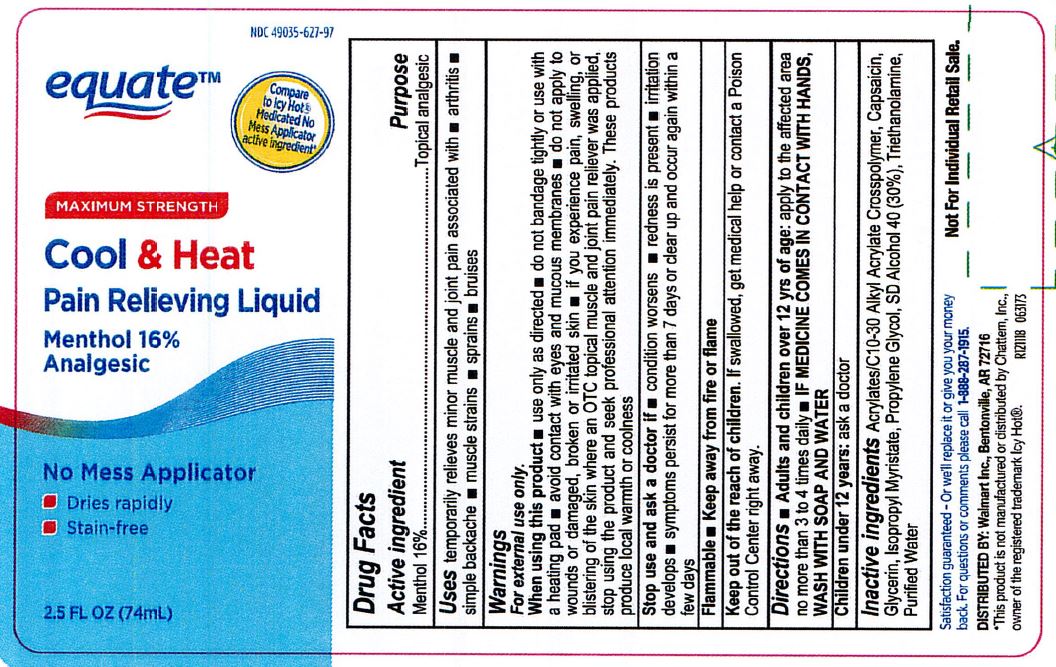 DRUG LABEL: Equate Cool and Heat Pain Relieving Liquid
NDC: 49035-627 | Form: LIQUID
Manufacturer: Walmart, Inc.
Category: otc | Type: HUMAN OTC DRUG LABEL
Date: 20201219

ACTIVE INGREDIENTS: MENTHOL 16 mg/100 mL
INACTIVE INGREDIENTS: ISOPROPYL MYRISTATE; GLYCERIN; WATER; (C10-C30)ALKYL METHACRYLATE ESTER; PROPYLENE GLYCOL; TROLAMINE; ALCOHOL; CAPSAICIN

Equate Cool & Heat Pain Relief

DOSAGE AND ADMINISTRATION

Adults and children over 12 yrs of age: apply to the affected area no more than 3 to 4 times daily

IF MEDICINE COMES IN CONTACT WITH HANDS, WASH WITH SOAP AND WATER.

When using this product: use only as directed. Do not bandage tightly or use with a heating pad. Avoid contact with eyes and mucous membranes. Do not apply to wounds or damaged, broken or irritated skin. If you experience pain, swelling, or blistering of the skin where an OTC topical muscle and joint pain reliever was applied, stop using the product and seek professional attention immediately. These products produce local warmth or coolness.

INACTIVE INGREDIENT

Acrylates/C10-30 Alkyl Acrylate Crosspolymer, Capsaicin, Glycerin, Isopropyl Myristate, Propylene Glycol, SD Alcohol 40 (30%Z), Triethanolamine, Purified Water.

INDICATIONS AND USAGE

Temporarily relieves minor muscle and joint pain associated with arthritis, simple backache, muscle strains, sprains, bruises.

Keep out of reach of children. If swallowed, get medical help or contact a Poison Control Center right away.

PURPOSE

Topical analgesic

ACTIVE INGREDIENT

Menthol 16%